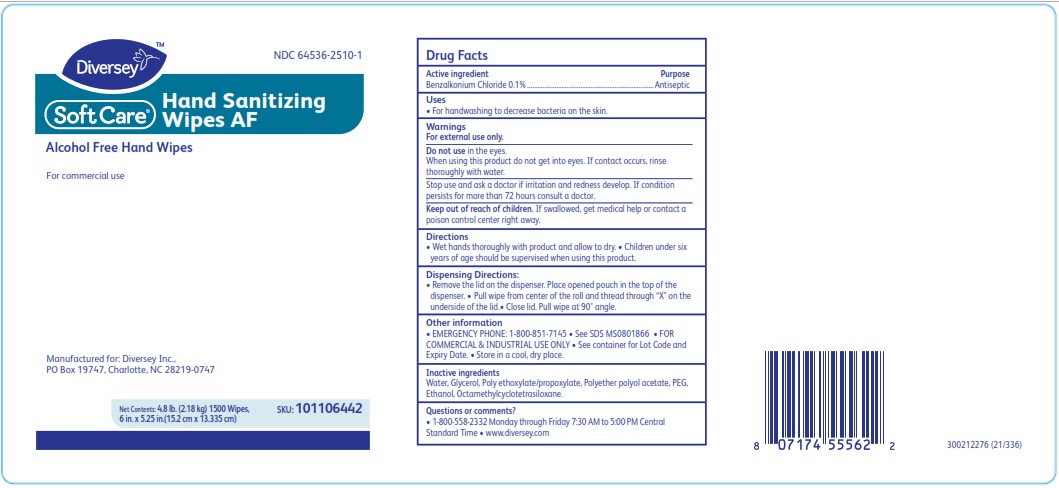 DRUG LABEL: Soft Care Hand Sanitizing Wipes AF
NDC: 64536-2510 | Form: CLOTH
Manufacturer: Diversey, Inc.
Category: otc | Type: HUMAN OTC DRUG LABEL
Date: 20220502

ACTIVE INGREDIENTS: BENZALKONIUM CHLORIDE 0.1 g/100 g
INACTIVE INGREDIENTS: WATER 79.4 g/100 g; GLYCERIN 12.5 g/100 g; PEG/PPG-18/18 DIMETHICONE 8 g/100 g

DOSAGE AND ADMINISTRATION

Remove the lid on the dispenser. Place opened pouch in the top of the dispenser. Pull wipe from center of the roll and thread through “X" on the underside of the lid. Close lid. Pull wipe at 90˚ angle

WARNINGS

For external use only. Do not use in the eyes.
When using this product do not get into eyes. If contact occurs, rinse
thoroughly with water.

INACTIVE INGREDIENT

Water, Glycerin, PEG/PPG-18/18 Dimethicone

INDICATIONS AND USAGE

Uses: For handwashing to decrease bacteria on the skin.

Keep out of reach of children. If swallowed, get medical help or contact a poison control center right away.

PURPOSE

Antiseptic

ACTIVE INGREDIENT

Benzalkonium Chloride 0.1%